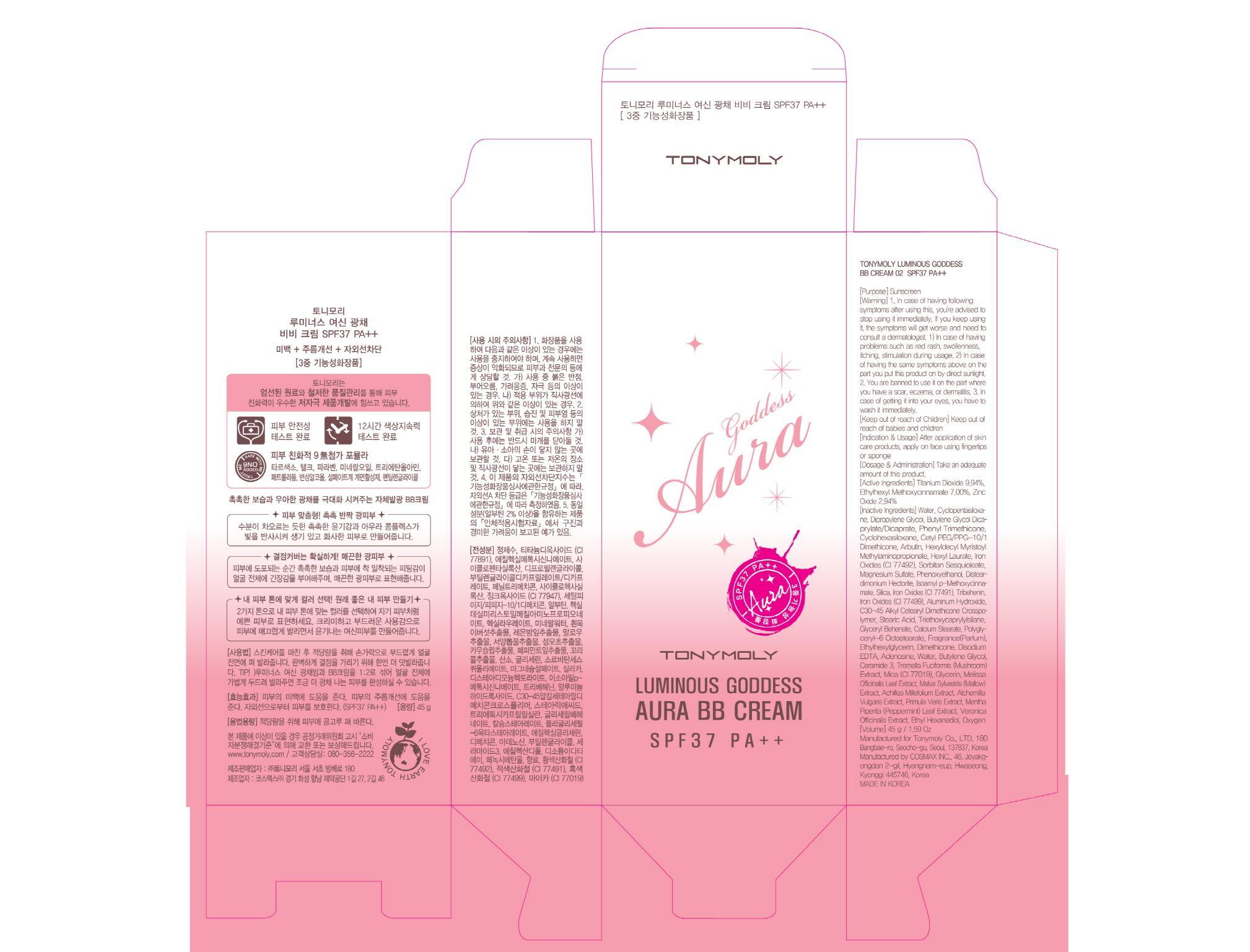 DRUG LABEL: TONYMOLY LUMINOUS GODDESS AURA BB
NDC: 59078-052 | Form: CREAM
Manufacturer: Tonymoly Co., Ltd.
Category: otc | Type: HUMAN OTC DRUG LABEL
Date: 20150303

ACTIVE INGREDIENTS: Titanium Dioxide 4.47 g/45 g; Octinoxate 3.15 g/45 g; Zinc Oxide 1.32 g/45 g
INACTIVE INGREDIENTS: Water; Dipropylene Glycol

ACTIVE INGREDIENT

Active Ingredients: Titanium Dioxide 9.94%, Ethylhexyl Methoxycinnamate 7.00%, Zinc Oxide 2.94%

INACTIVE INGREDIENT

Inactive Ingredients: Water, Cyclopentasiloxane, Dipropylene Glycol, Butylene Glycol Dicaprylate/Dicaprate, Phenyl Trimethicone, Cyclohexasiloxane, Cetyl PEG/PPG-10/1 Dimethicone, Arbutin, Hexyldecyl Myristoyl Methylaminopropionate, Hexyl Laurate, Iron Oxides (CI 77492), Sorbitan Sesquioleate, Magnesium Sulfate, Phenoxyethanol, Disteardimonium Hectorite, Isoamyl p-Methoxycinnamate, Silica, Iron Oxides (CI 77491), Tribehenin, Iron Oxides (CI 77499), Aluminum Hydroxide, C30-45 Alkyl Cetearyl Dimethicone Crosspolymer, Stearic Acid, Triethoxycaprylylsilane, Glyceryl Behenate, Calcium Stearate, Polyglyceryl-6 Octastearate, Fragrance(Parfum), Ethylhexylglycerin, Dimethicone, Disodium EDTA, Adenosine, Water, Butylene Glycol, Ceramide 3, Tremella Fuciformis (Mushroom) Extract, Mica (CI 77019), Glycerin, Melissa Officinalis Leaf Extract, Malva Sylvestris (Mallow) Extract, Achillea Millefolium Extract, Alchemilla Vulgaris Extract, Primula Veris Extract, Mentha Piperita (Peppermint) Leaf Extract, Veronica Officinalis Extract, Ethyl Hexanediol, Oxygen

PURPOSE

Purpose: Sunscreen

WARNINGS

Warning: 1. In case of having following symptoms after using this, you're advised to stop using it immediately. If you keep using it, the symptoms will get worse and need to consult a dermatologist. 1) In case of having problems such as red rash, swollenness, itching, stimulation during usage. 2) In case of having the same symptoms above on the part you put this product on by direct sunlight. 2. You are banned to use it on the part where you have a scar, eczema, or dermatitis. 3. In case of getting it into your eyes, you have to wash it immediately.

Keep out of reach of Children: Keep out of reach of babies and children

INDICATIONS & USAGE

Indication & Usage: After application of skin care products, apply on face using fingertips or sponge.

DOSAGE & ADMINISTRATION

Dosage & Administration: Take an adequate amount of this product.

PACKAGE LABEL.PRINCIPAL DISPLAY PANEL

Image of carton